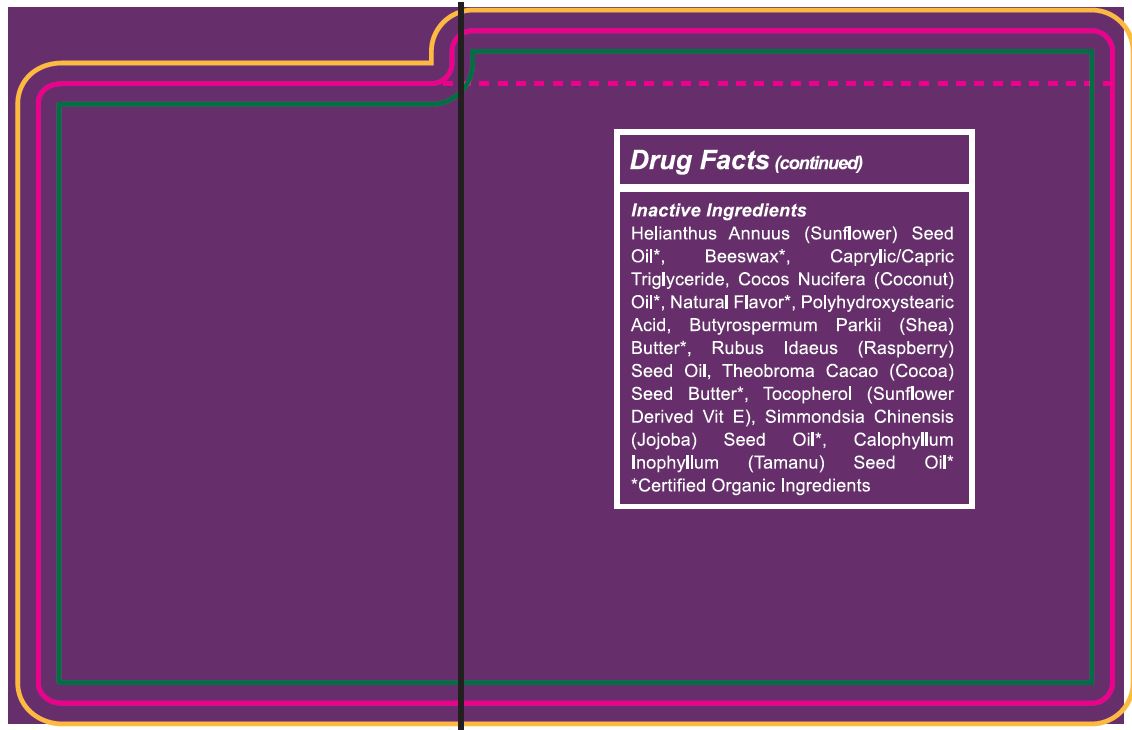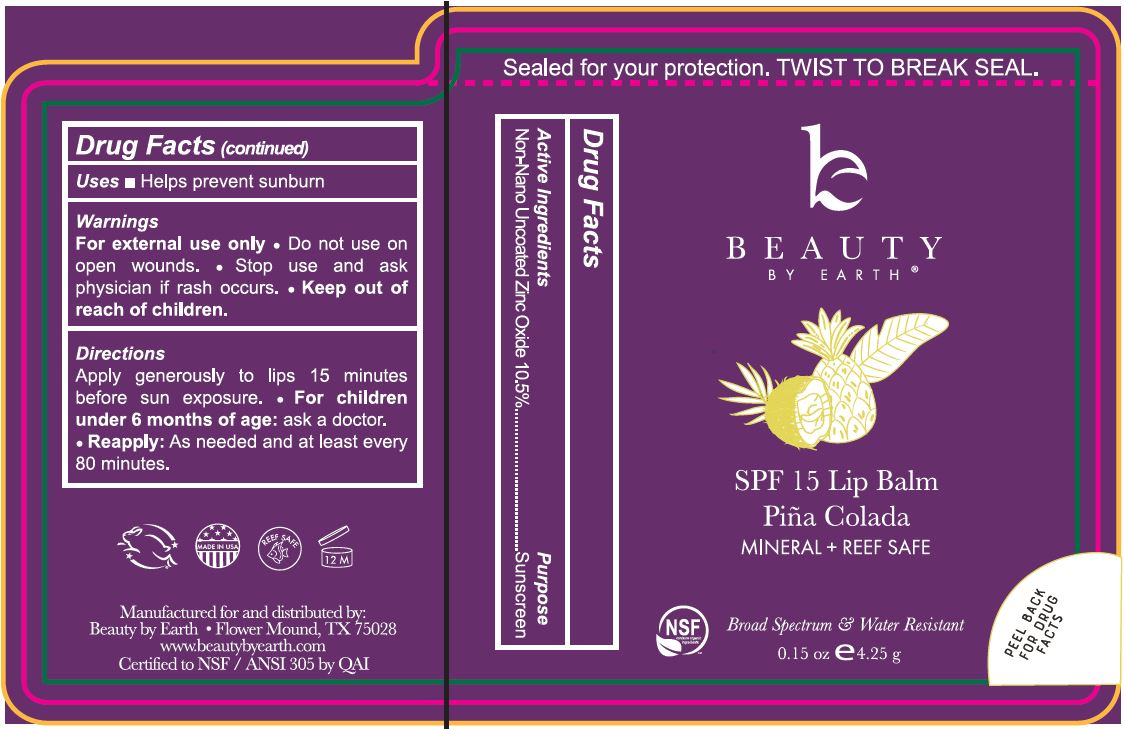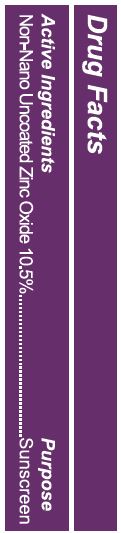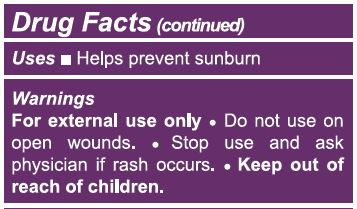 DRUG LABEL: Zinc Oxide Lip Balm Pina Colada
NDC: 62932-226 | Form: STICK
Manufacturer: Private Label Select Ltd CO
Category: otc | Type: HUMAN OTC DRUG LABEL
Date: 20201229

ACTIVE INGREDIENTS: ZINC OXIDE 10 g/100 g
INACTIVE INGREDIENTS: .BETA.-TOCOPHEROL; .GAMMA.-TOCOPHEROL; JOJOBA OIL; POLYHYDROXYSTEARIC ACID (2300 MW); COCONUT OIL; SHEA BUTTER; RASPBERRY SEED OIL; COCOA BUTTER; POLYHYDROXYSTEARIC ACID STEARATE; MEDIUM-CHAIN TRIGLYCERIDES; .ALPHA.-TOCOPHEROL, D-; .DELTA.-TOCOPHEROL; TAMANU OIL; WHITE WAX; SUNFLOWER OIL

Beauty By Earth SPF 15 Lip Balm Pina Colada